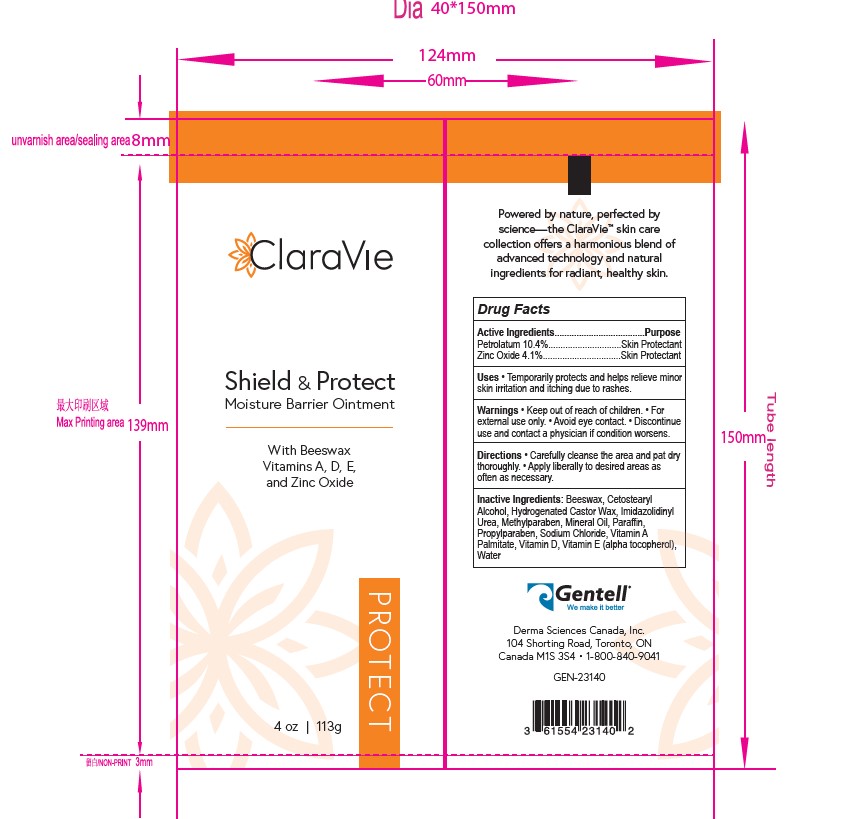 DRUG LABEL: Shield and Protect Barrier Cream
NDC: 61554-500 | Form: CREAM
Manufacturer: Gentell LLC
Category: otc | Type: HUMAN OTC DRUG LABEL
Date: 20241008

ACTIVE INGREDIENTS: ZINC OXIDE 4.13 g/100 g; PETROLATUM 10.32 g/100 g
INACTIVE INGREDIENTS: PARAFFIN; CHOLECALCIFEROL 0.05 g/100 g; VITAMIN A PALMITATE 0.03 g/100 g; SODIUM CHLORIDE 0.48 g/100 g; HYDROGENATED CASTOR OIL 0.36 g/100 g; LIGHT MINERAL OIL 20.64 g/100 g; WATER 59.52 g/100 g; PROPYLPARABEN 0.1 g/100 g; IMIDUREA 0.3 g/100 g; METHYLPARABEN 0.25 g/100 g; CETOSTEARYL ALCOHOL 3.44 g/100 g; SYNTHETIC BEESWAX 0.36 g/100 g

Sheild and Protect Moisture Barrier Ointment

Active Ingredients

Zinc Oxide

Petrolatum

Keep out of rach of children

Keep out of reach of Children

Inactive Ingredients

Purified water

Mineral Oil

Sodium Chloride

Hydrogenated Castor Wax

Beeswax

Imidazolidinyl Urea

Paraffin

Propylparaben

Methylparaben

Vitamin A Palmitate

Cetostearyl alcohol

Vitamin D

Vitamin E(alpha tocopherol)

Purpose

Gentell Shield & Protect Moisture Barrier Cream forms a water-shedding shield thta helps soothe and protect dry or irritated skin. Theraprutic against irritation from urine, feces, and other bodily secretions. Sheild & Protect leaves skin soft and smooth rather than irretated and greasy. Ideal for sensitive skin.

Warnings

For external use only

Avoid eye contact

Discontinue use and contact a physiciean if condition worsens, or symptoms persist from more than seven days

Keep this out of the reah of children

Dosage & Administration

Carefully cleanse the area and pat dry thoroughly. Apply liberally to desired areas as often as necessary or when prolonged wxposure is anticipated.

Indication and usage

Shield & Protect Moisture Barrier Cream helps restore, replenish and soothe ry irritated or otherwise compromised skin.

It helps treat or pevent minor skin irritations assoiated with incontinence.

Protects fom and seals out wetness

Primary Label

4oz

Shield and Protect